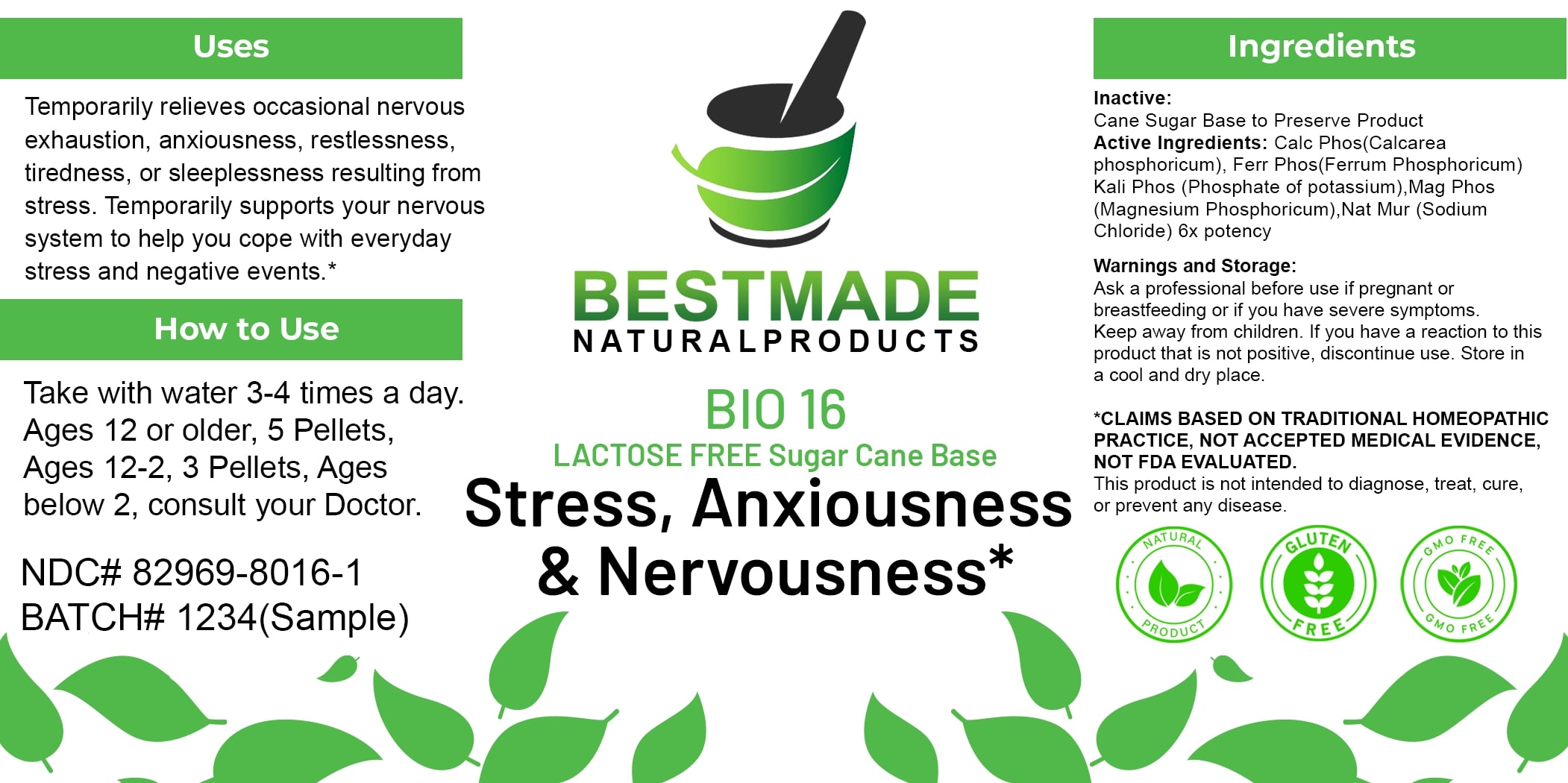 DRUG LABEL: Bestmade Natural Products BIO16 Lactose Free
NDC: 82969-8016 | Form: TABLET, SOLUBLE
Manufacturer: Bestmade Natural Products
Category: homeopathic | Type: HUMAN OTC DRUG LABEL
Date: 20250313

ACTIVE INGREDIENTS: TRIBASIC CALCIUM PHOSPHATE 6 [hp_X]/6 [hp_X]; SODIUM CHLORIDE 6 [hp_X]/6 [hp_X]; MAGNESIUM PHOSPHATE, DIBASIC TRIHYDRATE 6 [hp_X]/6 [hp_X]; FERROSOFERRIC PHOSPHATE 6 [hp_X]/6 [hp_X]; DIBASIC POTASSIUM PHOSPHATE 6 [hp_X]/6 [hp_X]
INACTIVE INGREDIENTS: SUCROSE 6 [hp_X]/6 [hp_X]

BIO16 Stress, Anxiousness & Nervousness* LACTOSE FREE Sugar Cane Base

DOSAGE AND ADMINISTRATION

How to Use

Take with water 3-4 times a day. Ages 12 or older, 5 Pellets, Ages 12-2, 3 Pellets, Ages below 2, consult your Doctor.

Inactive:

Cane Sugar Base to Preserve Product

Active Ingredients:

Calc Phos (Calcarea phosphoricum), Ferr Phos (Ferrum Phosphoricum) Kali Phos (Phosphate of potassium), Mag Phos (Magnesium Phosphoricum), Nat Mur (Sodium Chloride) 6x potency

Uses

Temporarily relieves occasional nervous exhaustion, anxiousness, restlessness, tiredness, or sleeplessness resulting from stress. Temporarily supports your nervous system to help you cope with everyday stress and negative events.*

*CLAIMS BASED ON TRADITIONAL HOMEOPATHIC PRACTICE, NOT ACCEPTED MEDICAL EVIDENCE, NOT FDA EVALUATED.

This product is not intended to diagnose, treat, cure, or prevent any disease.

Uses

Temporarily relieves occasional nervous exhaustion, anxiousness, restlessness, tiredness, or sleeplessness resulting from stress. Temporarily supports your nervous system to help you cope with everyday stress and negative events.*

*CLAIMS BASED ON TRADITIONAL HOMEOPATHIC PRACTICE, NOT ACCEPTED MEDICAL EVIDENCE, NOT FDA EVALUATED.

This product is not intended to diagnose, treat, cure, or prevent any disease.

KEEP OUT OF REACH OF CHILDREN

Warnings and Storage:

Ask a professional before use if pregnant or breastfeeding or if you have severe symptoms. Keep away from children. If you have a reaction to this product that is not positive, discontinue use. Store in a cool and dry place.

Warnings and Storage:

Ask a professional before use if pregnant or breastfeeding or if you have severe symptoms. Keep away from children. If you have a reaction to this product that is not positive, discontinue use. Store in a cool and dry place.

*CLAIMS BASED ON TRADITIONAL HOMEOPATHIC PRACTICE, NOT ACCEPTED MEDICAL EVIDENCE NOT FDA EVALUATED.

This product is not intended to diagnose, treat, cure, or prevent any disease.

Entire package label